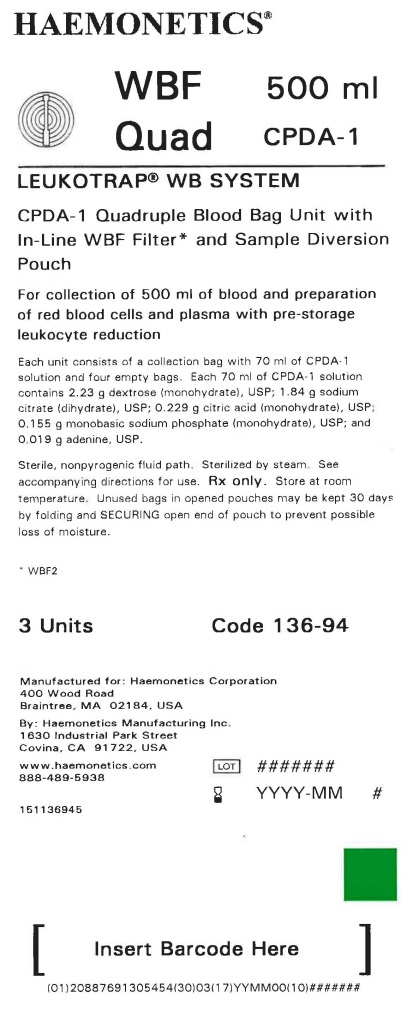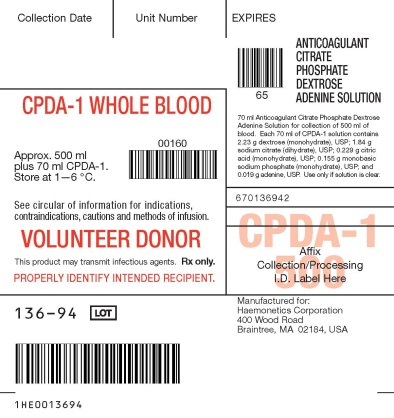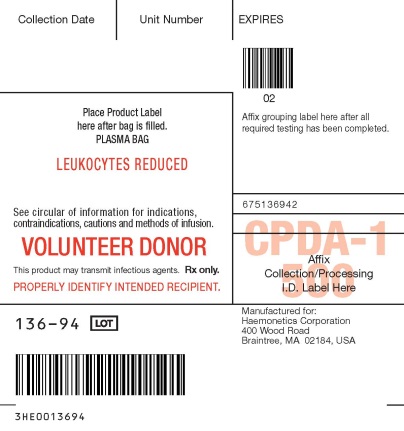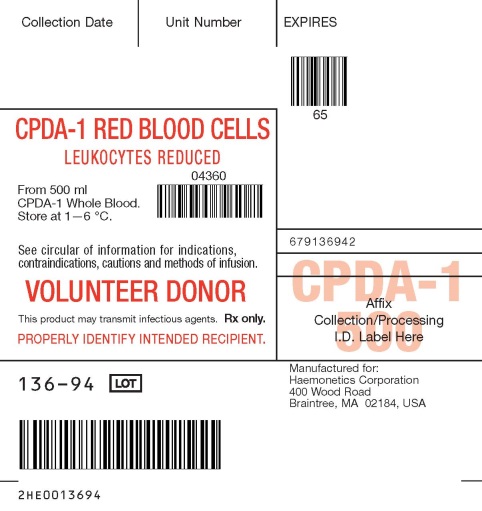 DRUG LABEL: Leukotrap WB System
NDC: 53157-136 | Form: SOLUTION
Manufacturer: Haemonetics Corporation
Category: prescription | Type: HUMAN PRESCRIPTION DRUG LABEL
Date: 20200102

ACTIVE INGREDIENTS: DEXTROSE MONOHYDRATE 2.23 g/70 mL; SODIUM CITRATE 1.84 g/70 mL; CITRIC ACID MONOHYDRATE 0.229 g/70 mL; SODIUM PHOSPHATE, MONOBASIC, MONOHYDRATE 0.155 g/70 mL; ADENINE 0.019 g/70 mL

Leukotrap WB System, CPDA-1 Blood Collection Set with WBF2 Filter and Sampling System

DESCRIPTION

CPDA-1 Blood Collection Set, Quadruple Bag with WBF2 Filter and Sampling System

Instruction for Use for Systems Containing a Y Sampling Site (YSS) or Sample Diversion Pouch (with or without a pre-attached Samp Lok Vacuum Tube Holder). Refer to unit foil package label for specific product description being used.

Sterile, nonpyrogenic fluid path. Sterilized by steam.

Rx only.

This product is free of natural rubber latex.

INDICATIONS AND USAGE

Indicated for collection of blood and preparation of red blood cells and plasma with pre-storage leukocyte reduction. Platelet concentrates are not intended to be made with this product.

WARNINGS

Failure to achieve and maintain a closed system during processing would result in a product that must be transfused within 24 hours.

GENERALPRECAUTIONS

Use Aseptic Technique.

Use only if solution is clear.

Store CPDA-1 preserved red blood cells at 1—6 °C for up to 35 days and use as indicated.

* During processing, always observe the following precautions:

1. Sealing should be done in a manner that avoids fluid splatter.

2. Always dispose of blood-contaminated products in a manner consistent with established BIOHAZARD safety procedures.

ADVERSE REACTIONS

There are no known potential adverse reactions associated specifically with the Leukotrap WB System with CPDA-1.

I. BLOOD COLLECTION INSTRUCTIONS FOR SYSTEMS CONTAINING A Y SAMPLING SITE (YSS) ONLY

1. Load blood agitation device or suspend blood bag on donor scale and adjust donor scale to desired collection gross weight as per manufacturer's instructions.

2. Clamp donor tubing between the Donor Care® Needle Guard (DCNG) and Y Sampling Site.

3. Secure donor tubing above the Y connector and disinfect site of phlebotomy.

4. If using blood pressure cuff, inflate to not more than 60 mm Hg.

5. Remove donor needle cover and accomplish phlebotomy.

6. Release clamp and ensure there is blood flow. Reduce pressure as required.

7. Slide the DCNG midway over the needle hub and securely tape DCNG to the donor's arm as close to the top of the DCNG as possible. Note: If blood flow is slow, slide DCNG away from the needle hub, adjust and re-engage DCNG. If repeated needle adjustment is necessary, slide DCNG away from the needle hub and re-engage at the end of blood collection.

8. Collect appropriate volume of blood into collection bag, as indicated on packaging.

Note: Mix blood and anticoagulant frequently during collection, for example, once every 45 seconds, and immediately after collection. If blood agitation device is used, follow manufacturer's operating instructions.

9. After required amount of blood has been collected, seal donor tubing between Y Sampling Site and the collection bag.*

10. For blood sampling, remove the Y Sampling Site needle cover. Ensure the protective sheath is in place over the sampling needle.

11. Fasten the vacuum tube holder on to the base of the sampling needle.

12. Collect blood samples into vacuum tubes.

13. Ensure the vacuum tubes are centered within the vacuum tube holder during sample collection.

14. Maintain forward pressure on the vacuum tubes during sample collection.

Note: After the last tube is collected, it is recommended that the vacuum tube holder be left in place.

15. After blood samples are collected, clamp donor tubing between the Y Sampling Site and DCNG, as close as possible to the DCNG.

16. Release any remaining pressure from the donor's arm.

17. DCNG must be held stationary while the needle is withdrawn into it. While holding sides of DCNG near the front, grasp the tubing below the clamp and pull the needle into the DCNG until it locks into place, and the needle hub engages the bottom of the DCNG.

18. Insert the DCNG into the vacuum tube holder. Note: It is recommended that the DCNG be inserted securely into the vacuum tube holder prior to discarding.

19. Seal donor tubing adjacent to DCNG.* Detach and discard needle, DCNG, Y Sampling Site and tubing.*

20. Strip tubing between seal and collection bag.

21. Continue to “Processing Instructions”, Section IV, Step 1.

II. BLOOD COLLECTION INSTRUCTION FOR SYSTEMS CONTAINING A SAMPLE DIVERSION POUCH WITH OR WITHOUT A PRE-ATTACHED SAMP LOK® VACUUM TUBE HOLDER

When using systems with a pre-attached Samp Lok vacuum tube holder, follow instructions as noted below, but refer to Section III when indicated to do so.

1. Load blood agitation device or suspend blood bag on donor scale and adjust donor scale to desired collection gross weight as per manufacturer's instructions.

2. Clamp donor tubing between the Donor Care® Needle Guard (DCNG) and Sampling Site.

3. Secure donor tubing above the Y connector and disinfect site of phlebotomy.

4. If using blood pressure cuff, inflate to not more than 60 mm Hg.

5. Remove donor needle cover and accomplish phlebotomy.

6. Release clamp and ensure there is blood flow.

7. Slide the DCNG midway over the needle hub and securely tape DCNG to the donor's arm as close to the top of the DCNG as possible. Note: If blood flow is slow, slide DCNG away from the needle hub, adjust and re-engage DCNG. If repeated needle adjustment is necessary, slide DCNG away from the needle hub and re-engage at the end of blood collection.

8. The donor blood will be automatically diverted to the sample diversion pouch. Once the sample diversion pouch is filled, close clamp immediately on tubing between the sample diversion pouch and Y connector. Warning: To avoid risk of air embolism to donor, do not squeeze sample diversion pouch while tubing is open.

9. Open snap-open closure between the Y connector and the collection bag to initiate blood collection. Reduce pressure as needed.

10. Permanently seal tubing between the sample diversion pouch and the Y connector to maintain sterility of the system prior to collecting blood samples.* Note: When using systems with a pre-attached Samp Lok vacuum tube holder, go to Section III.

11. For blood sampling, remove the Sampling Site needle cover. Ensure the protective sheath is in place over the sampling needle.

12. Fasten the vacuum tube holder on to the base of the sampling needle.

13. Position the sample diversion pouch downwards so that the air rises to the top of the pouch and away from the vacuum tube holder. Note: Drawing air into the vacuum tube may cause hemolysis.

14. Collect blood samples from the sample diversion pouch into vacuum tubes within approximately four minutes to avoid possible clot formation.

15. Ensure the vacuum tubes are centered within the vacuum tube holder during sample collection.

16. Maintain forward pressure on the vacuum tubes during sample collection.

Note: After the last tube is collected, it is recommended that the vacuum tube holder be left in place.

17. Collect appropriate volume of blood into collection bag as indicated on packaging.

Note: Mix blood and anticoagulant frequently during collection, for example, once every 45 seconds, and immediately after collection. If blood agitation device is used, follow manufacturer's operating instructions.

18. After required amount of blood has been collected, seal donor tubing close to snap open closure.* Note: If pre-filtration quality control is to be performed, leave an adequate length (~10 inches) of QC tubing containing anticoagulated blood attached to the collection bag.

19. Clamp donor tubing between the Y connector and DCNG, as close as possible to the DCNG.

20. Release any remaining pressure from the donor's arm.

21. DCNG must be held stationary while the needle is withdrawn into it. While holding sides of DCNG near the front, grasp the tubing below the clamp and pull the needle into the DCNG until it locks into place, and the needle hub engages the bottom of the DCNG.

22. Insert the DCNG into the vacuum tube holder, if desired. Note: It is recommended that the DCNG be inserted securely into the vacuum tube holder prior to discarding.

23. Seal donor tubing adjacent to DCNG.* Detach and discard needle, DCNG, sample diversion pouch and tubing.*

24. Strip tubing between seal and collection bag.

25. Continue to "Processing Instructions", Section IV, Step 1.

III. WHEN USING SYSTEMS WITH A PRE-ATTACHED SAMP LOK® VACUUM TUBE HOLDER

1. To collect blood samples, open lid from Samp Lok vacuum tube holder.

2. Open snap-open closure between sample diversion pouch and Samp Lok vacuum tube holder.

3. Position the sample diversion pouch downwards so that the air rises to the top of the pouch and away from the Samp Lok vacuum tube holder. Note: Drawing air into the vacuum tube may cause hemolysis.

4. Collect blood samples from the sample diversion pouch into vacuum tubes within approximately four minutes to avoid possible clot formation.

5. Ensure the vacuum tubes are centered within the Samp Lok vacuum tube holder during sample collection.

6. Maintain forward pressure on the vacuum tubes during sample collection.

7. The lid may be closed on the Samp Lok vacuum tube holder after sample collection.

8. Return to Section II, Step 17. Note: When collection of unit is complete and the donor needle is engaged in the DCNG, open the lid of the Samp Lok vacuum tube holder and insert the DCNG into the holder. Twist until it locks into place. An audible click will confirm that it is locked.

IV. Blood Filtration Instructions

1. Filter and process whole blood within 72 hours of collection.

2. Mix whole blood/anticoagulant gently and thoroughly.

- 3. Place empty red cell storage bag on a horizontal surface.
- 4. Ensure cap of blood recovery vent above the filter is tightly closed.
- 5. Hang whole blood bag up to 60 inches (1.52 meters) above empty red cell storage bag and ensure filter is vertical. Note: The maximum head height should be 60 inches (1.52 meters) for whole blood filtered at room temperature and at 1—6 °C.
- 6. Open snap-open closure of whole blood bag. Priming will occur automatically by gravity.
- 7. After blood fills one side of the air vent below the filter, open snap-open closure immediately below the air vent to begin filtration.
- 8. Allow blood to filter by gravity. Note: Do not apply mechanical or manual pressure to increase flow rate. Filtration is complete when whole blood bag is empty.
- 9. Remove cap from blood recovery vent above the filter and allow the upstream side (non-printed side) of the filter to drain.
- 10. When the upstream side of the filter is empty, clamp tubing below the filter. Note: Filtration times can be influenced by collection and processing conditions and biological variability of donors. Experimental data with some filter products indicate that a prolonged filtration can be an indication of sub-optimal leukocyte reduction.
- 11. Seal tubing just below the snap-open closure.*
- 12. Detach and discard collection bag and filter.* Note: Do not strip tubing prior to sealing tubing. If it is desired to strip blood from numbered tubing, do so only after tubing has been sealed close to the snap-open closure and detached.
- 13. If desired, seal at or adjacent to "X" marks on the tubing to provide numbered segments of anticoagulated blood for typing or crossmatching.* Notes: If it is necessary to strip blood from numbered tubing for re-suspension, care should be taken when stripping is performed. Increased (mechanical) hemolysis has been associated with stripping when blood is cold and has a higher hematocrit. Do not strip forcefully or frequently against a snap-open closure.

V. PROCESSING INSTRUCTIONS

- 1. Load whole blood and remaining bags into centrifuge cup, ensuring that the tubing stays in the top half of the cup.
- 2. Centrifuge at conditions designed to produce desired components.
- 3. Carefully remove the unit from the centrifuge and place the collection bag in the plasma expressor.
- 4. Clamp tubing to extra satellite bag(s), if present.
- 5. Gently apply expressor pressure.
- 6. Open snap-open closure on collection bag and express plasma.
- 7. After plasma is expressed, clamp tubing between satellite bag(s) whole blood bag and release expressor pressure.
- 8. Seal tubing and detach the bag containing packed red cells, and set aside plasma for further processing.* Note: If pre-filtration quality control is to be performed, leave an adequate length (~10 inches) of QC tubing containing anticoagulated blood attached to the collection bag.
- 9. Gently mix packed red cells.
- 10. Store CPDA-1 preserved red blood cells at 1—6 °C for up to 35 days and use as indicated.

HOW SUPPLIED

Each shipping case contains 6 foil envelopes. Within each foil envelope resides 3 units of the collection system. Each unit consists of a collection bag with 70 ml of CPDA-1 solution and two empty bags.

REFERENCES

HAEMONETICS and THE Blood Management Company are trademarks of Haemonetics Corporation.

DonorCare and SampLok are registered trademarks of ITL Corporation, Canberra, Australia.

Manufactured for:

Haemonetics Corporation

400 Wood Road

Braintree, MA 02184, USA

By: Haemonetics Manufacturing Inc.

1630 Industrial Park Street

Covina, CA 91722, USA

www.haemonetics.com

800-537-2802

PACKAGE/LABEL PRINCIPAL DISPLAY PANEL

Envelope Label

Collection Bag Label

Plasma Bag Label

Transfer Bag Label